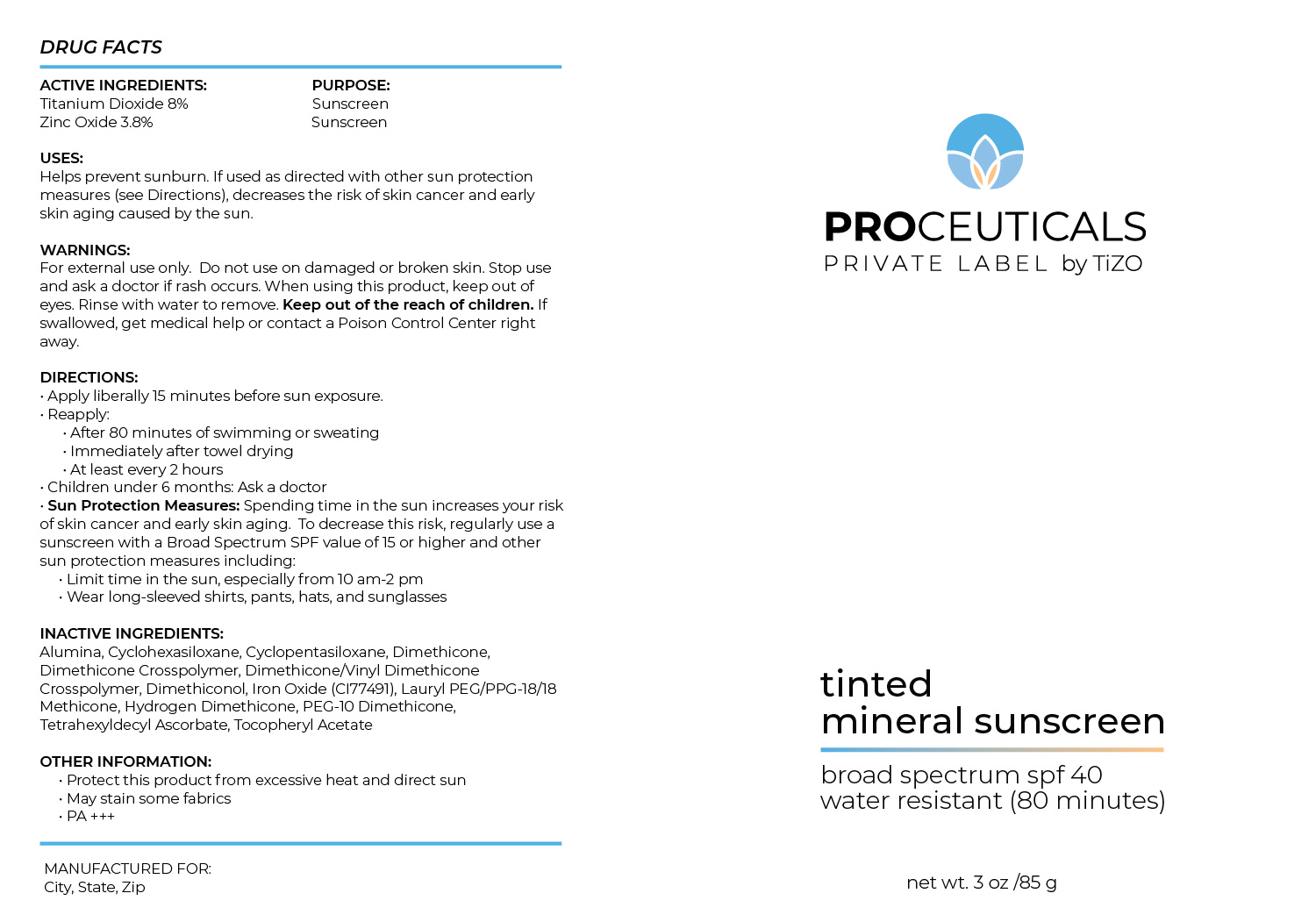 DRUG LABEL: Proceuticals Private Label by TiZO Tinted Facial Mineral Sunscreen Backbar
NDC: 58892-201 | Form: CREAM
Manufacturer: Fallien Cosmeceuticals, LTD
Category: otc | Type: HUMAN OTC DRUG LABEL
Date: 20250117

ACTIVE INGREDIENTS: TITANIUM DIOXIDE 80 mg/1 g; ZINC OXIDE 38 mg/1 g
INACTIVE INGREDIENTS: ALUMINA; .ALPHA.-TOCOPHEROL ACETATE; HYDROGEN DIMETHICONE (20 CST); IRON OXIDES; DIMETHICONOL (2000 CST); DIMETHICONE/VINYL DIMETHICONE CROSSPOLYMER (SOFT PARTICLE); CYCLOHEXASILOXANE; TETRAHEXYLDECYL ASCORBATE; DIMETHICONE; CYCLOPENTASILOXANE; DIMETHICONE CROSSPOLYMER; LAURYL PEG/PPG-18/18 METHICONE; PEG-10 DIMETHICONE (600 CST)

Active Ingredients:

Titanium Dioxide 8%

Zinc Oxide 3.8%

Warnings:

Stop use and ask a doctor if rash occurs.

Warnings:

Do not use on broken or damaged skin.

Warnings:

Keep out of the reach of children.

Purpose:

Sunscreen

Warnings:

Whe using this product, keep out of eyes.

Directions:

Apply liberally 15 minutes before sun exposure. Reapply after 80 minutes of swimming or sweating. Immediatley after towel drying. At leat every 2 hours.

Warnings:

For external use only. Do not use on damage or broken skin. Stop use and ask a doctor if rash occurs. When using this product, keep out of eyes. Rinse with water to remove. Keep out of the reach of children. If swallowed, get medical help or contact Poison Control Center right away.

Inactive Ingredients:

Alumina, Cyclohexasiloxane, Cyclopentasiloxane, Dimethicone, Dimethicone Crosspolymer, Dimethicone/Vinyl Dimethicone Crosspolymer, Dimethiconol, Iron Oxide (CI 77491), Lauryl PEG/PPG-18/18 Methicone, Hydrogen Dimethicone, PEG-10 Dimethicone, Tetrahexyldecyl Ascorbate, Tocopheryl Acetate

Uses:

Helps prevent sunburn if used as directed with other sun protection measures (see Directions), decreases the risk of skin cancer and early skin aging caused by the sun.